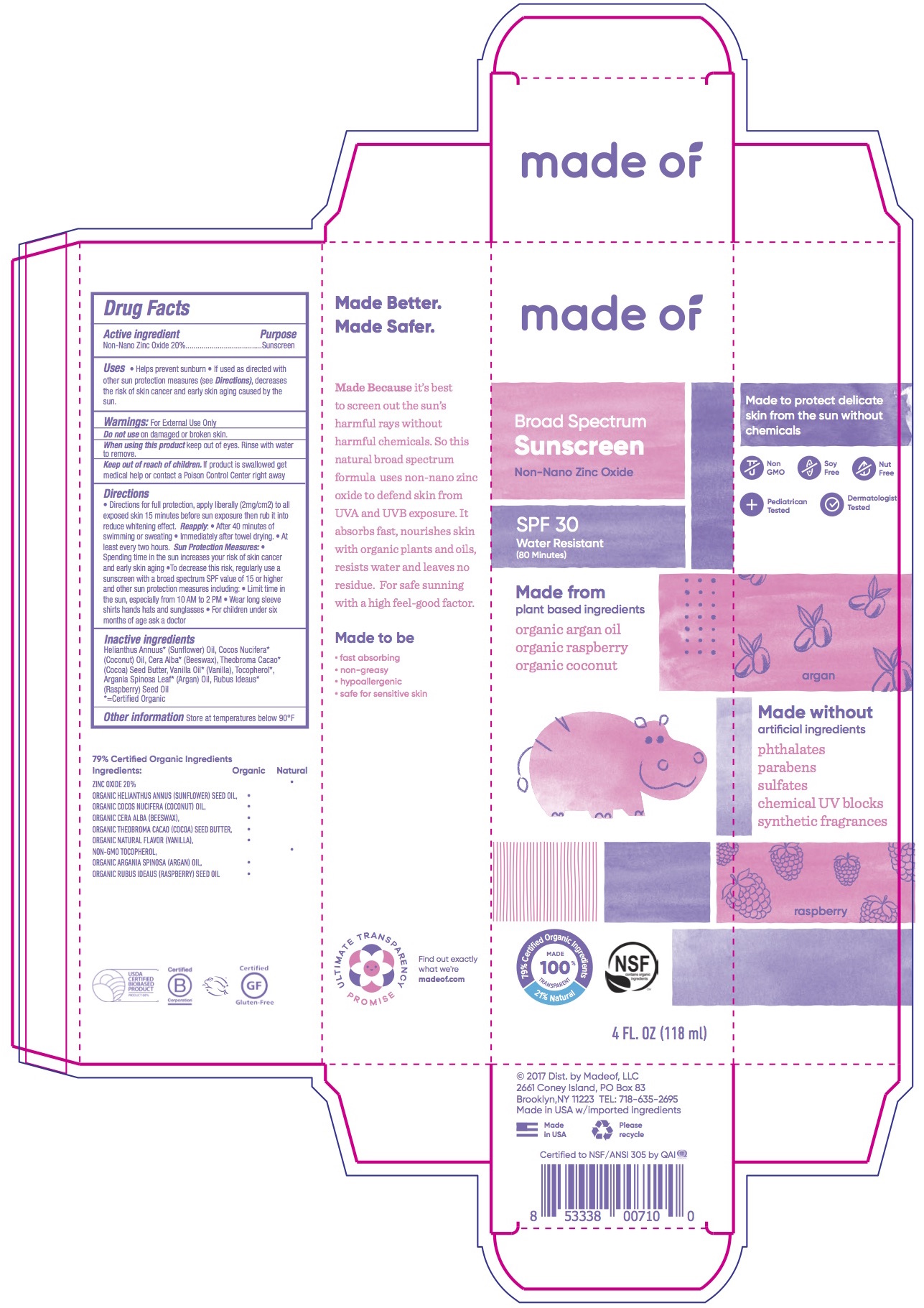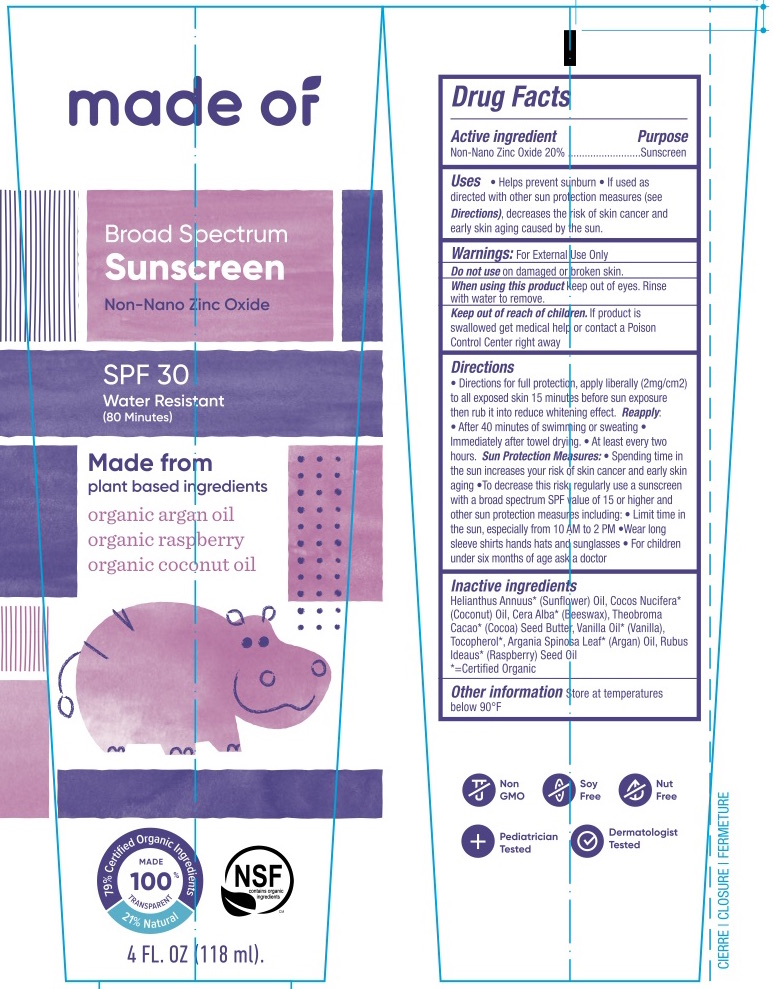 DRUG LABEL: made of Broad Spectrum SPF 30 Non-Nano Zinc Oxide Sunscreen
NDC: 71439-050 | Form: LOTION
Manufacturer: MADEOF, LLC
Category: otc | Type: HUMAN OTC DRUG LABEL
Date: 20200117

ACTIVE INGREDIENTS: ZINC OXIDE 20 g/100 mL
INACTIVE INGREDIENTS: VANILLA PLANIFOLIA OIL; ARGAN OIL; RASPBERRY SEED OIL; TOCOPHEROL; COCOA BUTTER; COCONUT OIL; SUNFLOWER OIL; YELLOW WAX

made of® Broad Spectrum SPF 30 Non-Nano Zinc Oxide Sunscreen

Drug Facts

Active Ingredient

Non-Nano Uncoated Zinc Oxide 20.0%

Purpose

Sunscreen

Uses

- Helps prevent sunburn
- If used as directed with other sun protection measures (see Directions), decreases the risk of skin cancer and early skin aging caused by the sun.

Warnings

For external use only.

Do not use on damaged or broken skin.

When using this product keep out of eyes. Rinse with water to remove.

Keep out of reach of children. If swallowed, get medical help or contact a poison control center right away.

Directions

- Diretions for full protection, apply liberally (2mg/cm2) to all exposed skin 15 minutes before sun exposure then rub it in to reduce whitening effect.

Reapply:

- After 40 minutes of swimming or sweating • Immediately after towel drying. • At least every two hours.

Sun Protection Measures:

- Spending time in the sun increases your risk of skin cancer and early skin aging
- To decrease this risk, regularly use a sunscreen with Broad Spectrum SPF value of 15 or higher and other sun protection measures including:
  - Limit time in the sun, especially from 10am-2pm
  - Wear long-sleeved shirts, pants, hats, and sunglasses
- For children under six months of age ask a doctor.

Ingredients

Helianthus Annuus* (Sunflower) Oil, Cocos Nucifera* (Coconut) Oil, Cera Alba* (Beeswax), Theobroma Cacao* (Cocoa) Seed Butter, Vanilla Oil* (Vanilla), Tocopherol*, Argania Spinosa Leaf* (Argan) Oil, Rubus Ideaus* (Raspberry) Seed Oil
*=Certified Organic

Other information:

Store at temperatures below 90°F

PRINCIPAL DISPLAY PANEL - 118 ml Tube

made of ®
Broad Spectrum Sunscreen

SPF 30
Water Resistant (80 minutes)

79% Certified Organic Ingredients

21% Natural

NSF

Non GMO

Soy Free

Nut Free

Pediatrician Tested

Dermatologist Tested

4 fl.oz (118 ml)